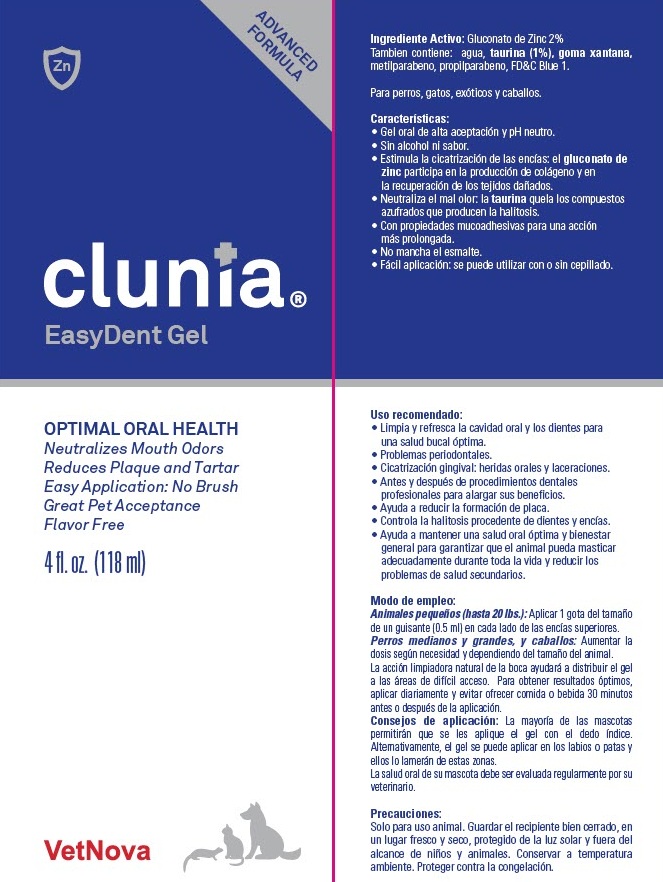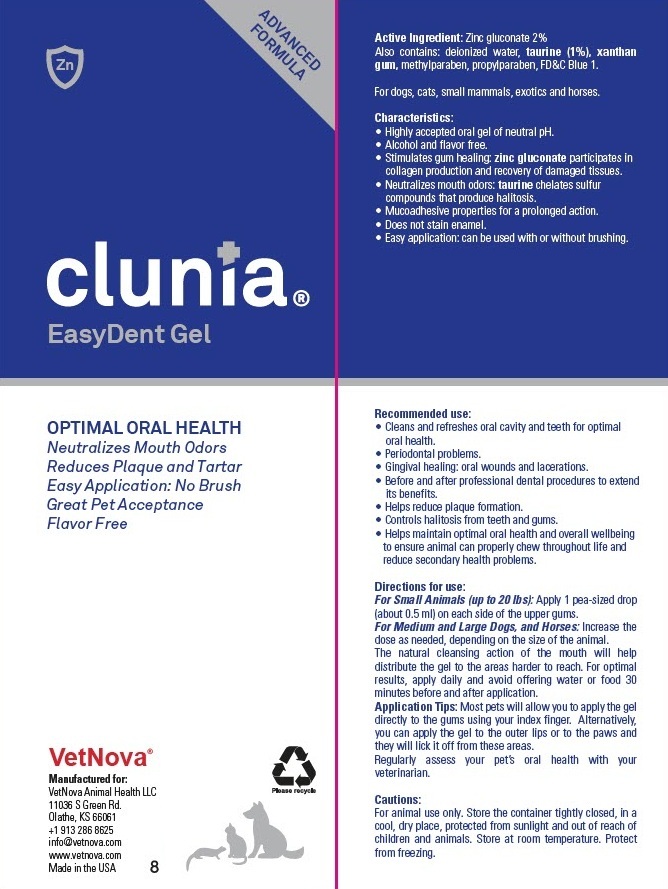 DRUG LABEL: Clunia EasyDent
NDC: 86145-600 | Form: LIQUID
Manufacturer: Vetnova Animal Health LLC
Category: animal | Type: OTC ANIMAL DRUG LABEL
Date: 20251117

ACTIVE INGREDIENTS: zinc gluconate 20 mg/1 mL
INACTIVE INGREDIENTS: XANTHAN GUM; taurine; WATER; Methylparaben; Propylparaben; FD&C BLUE NO. 1

Clunia® EasyDent Gel

Active Ingredient: Zinc gluconate 2%

Also contains: deionized water, taurine (1%), xanthan gum, methylparaben, propylparaben, FD&C Blue 1.

For dogs, cats, small mammals, exotics and horses.

VETERINARY INDICATIONS

Characteristics:

- Highly accepted oral gel of neutral pH.
- Alcohol and flavor free.
- Stimulates gum healing: zinc gluconate participates in collagen production and recovery of damaged tissues.
- Neutralizes mouth odors: taurine chelates sulfur compounds that produce halitosis.
- Mucoadhesive properties for a prolonged action.
- Does not stain enamel.
- Easy application: can be used with or without brushing.

INDICATIONS AND USAGE

Recommended use:

- Cleans and refreshes oral cavity and teeth for optimal oral health.
- Periodontal problems.
- Gingival healing: oral wounds and lacerations.
- Before and after professional dental procedures to extend its benefits.
- Helps reduce plaque formation.
- Controls halitosis from teeth and gums.
- Helps maintain optimal oral health and overall wellbeing to ensure animal can properly chew throughout life and reduce secondary health problems.

DOSAGE AND ADMINISTRATION

Directions for use:

For Small Animals (up to 20 lbs): Apply 1 pea-sized drop (about 0.5 ml) on each side of the upper gums.

For Medium and Large Dogs, and Horses: Increase the dose as needed, depending on the size of the animal. The natural cleansing action of the mouth will help distribute the gel to the areas harder to reach. For optimal results, apply daily and avoid offering water or food 30 minutes before and after application.

Application Tips: Most pets will allow you to apply the gel directly to the gums using your index finger. Alternatively, you can apply the gel to the outer lips or to the paws and they will lick it off from these areas.

Regularly assess your pet's oral health with your veterinarian.

PRECAUTIONS

Cautions:

For animal use only. Store the container tightly closed, in a cool, dry place, protected from sunlight and out of reach of children and animals. Store at room temperature. Protect from freezing.

PRINCIPAL DISPLAY PANEL - 118 ml Bottle Box

ADVANCED
FORMULA

clunia®
EasyDent Gel

OPTIMAL ORAL HEALTH

Neutralizes Mouth Odors
Reduces Plaque and Tartar
Easy Application: No Brush
Great Pet Acceptance
Flavor Free